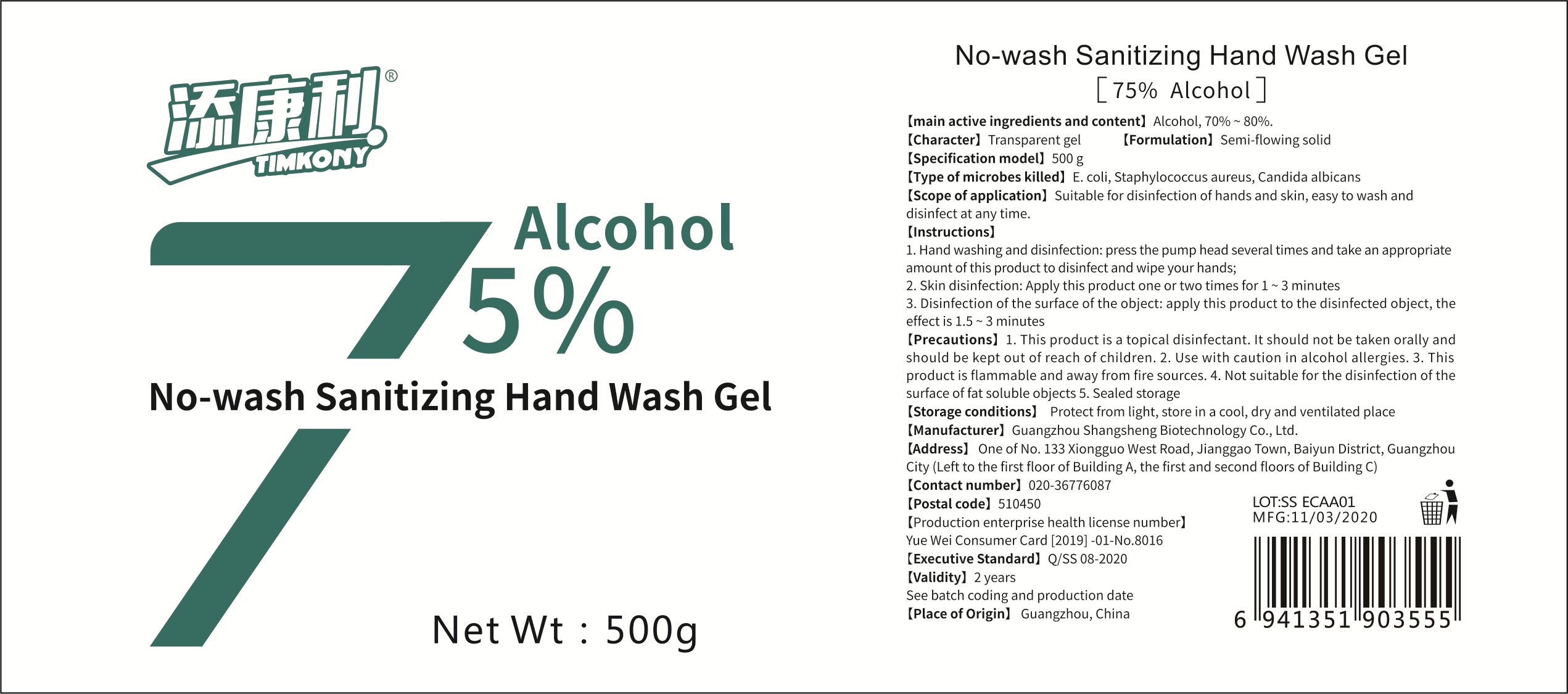 DRUG LABEL: No wash Sanitizing Hand Wash
NDC: 41864-001 | Form: GEL
Manufacturer: Guangzhou Shangsheng Biological Technology Co., Ltd.
Category: otc | Type: HUMAN OTC DRUG LABEL
Date: 20200401

ACTIVE INGREDIENTS: ALCOHOL 375 g/500 g
INACTIVE INGREDIENTS: WATER

DOSAGE AND ADMINISTRATION

Protect from light, store in a cool, dry and ventilated place

WARNINGS

This product is a topical disinfectant. It should not be taken orally and should be kept out of reach of children.

Use with caution in alcohol allergies.

This product is flammable and away from fire sources.

Not suitable for the disinfection of the surface of fat soluble objects 5. Sealed storage

ACTIVE INGREDIENT

alcohol

INACTIVE INGREDIENT

water

PURPOSE

Disinfection
Sterilization
No Rinseing

INDICATIONS AND USAGE

Hand washing and disinfection: press the pump head several times and take an appropriate amount of this product to disinfect and wipe your hands;

Skin disinfection: Apply this product one or two times for 1 ~ 3 minutes

Disinfection of the surface of the object: apply this product to the disinfected object, the effectis 1.5 ~ 3 minutes

keep out of reach of children